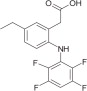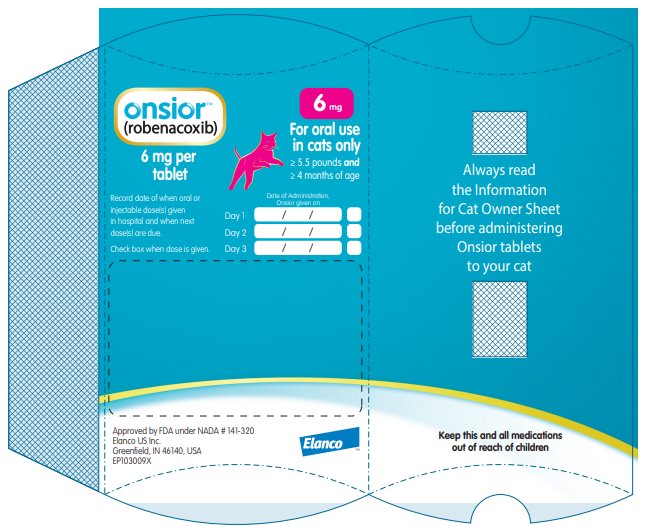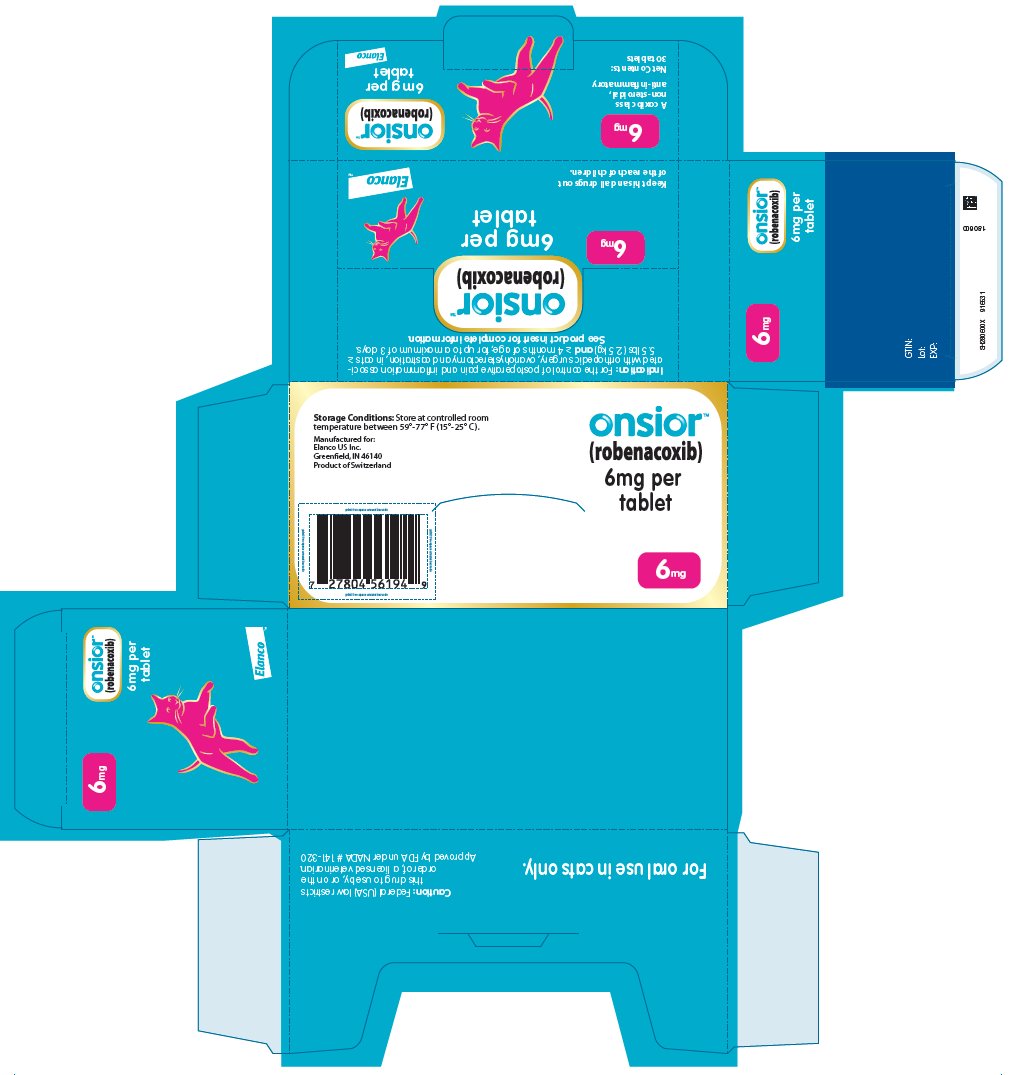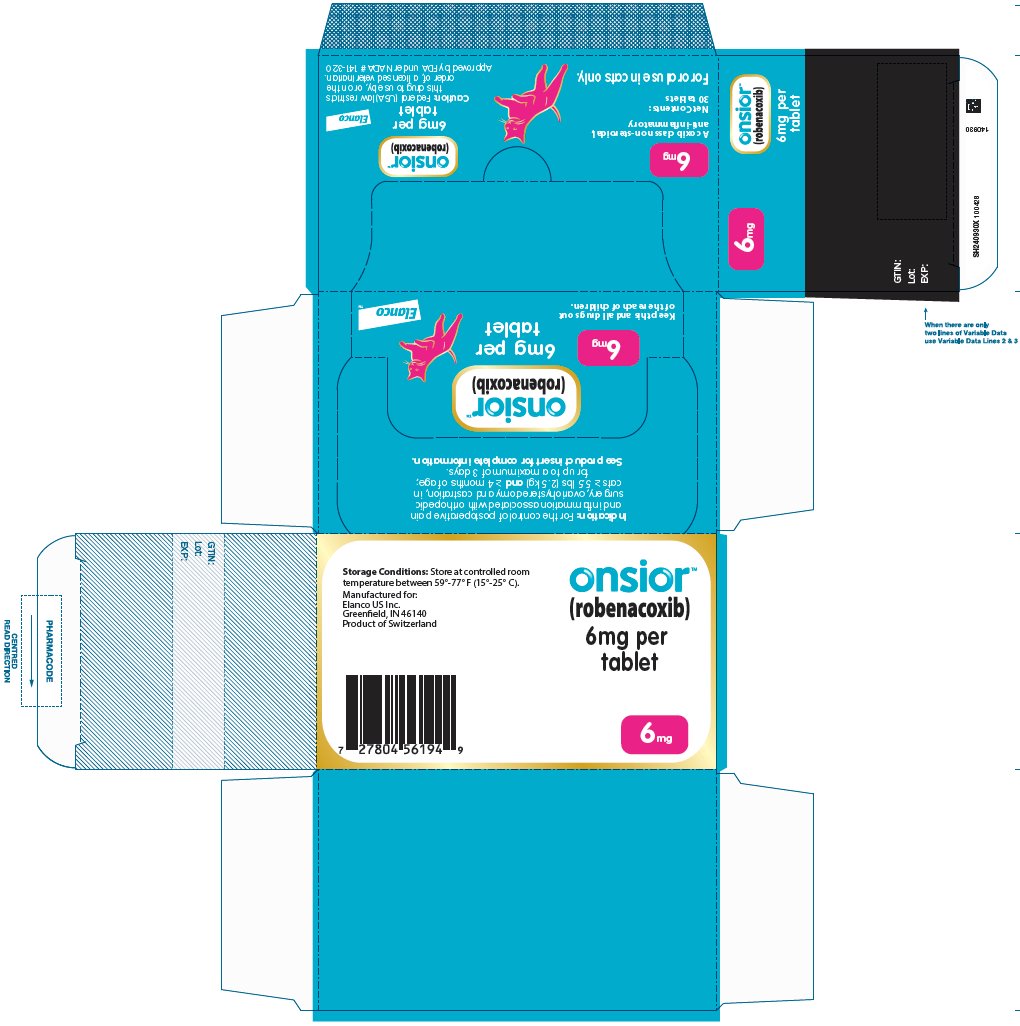 DRUG LABEL: Onsior
NDC: 58198-4875 | Form: TABLET
Manufacturer: Elanco US Inc.
Category: animal | Type: PRESCRIPTION ANIMAL DRUG LABEL
Date: 20241017

ACTIVE INGREDIENTS: robenacoxib 6 mg/1 1

onsior™
(robenacoxib)
6 mg Tablets for Cats

For Oral Use In Cats Only

Caution:

Federal (USA) law restricts this drug to use by or on the order of a licensed veterinarian.

Description:

ONSIOR (robenacoxib) is a non-narcotic, non-steroidal anti-inflammatory drug (NSAID) of the coxib class. Tablets are round, beige to brown in color, not scored, flavored and contain 6 mg robenacoxib. The molecular weight of robenacoxib is 327.28. The empirical formula is C16-H13-F4-NO2.

Robenacoxib is [5-Ethyl-2-(2,3,5,6-tetrafluoro-phenylamino)-phenyl]-acetic acid. The structural formula is:

Indication:

ONSIOR tablets are indicated for the control of postoperative pain and inflammation associated with orthopedic surgery, ovariohysterectomy and castration, in cats ≥ 5.5 lbs (2.5 kg) and ≥ 4 months of age; for up to a maximum of 3 days.

Dosage and Administration:

Always provide “Information for Cat Owners” Sheet with prescription. Carefully consider the potential benefits and risks of ONSIOR tablets and other treatment options before deciding to use ONSIOR tablets. Use the lowest effective dose for the shortest duration consistent with individual response.

The dose of ONSIOR tablets is 0.45 mg/lb (1 mg/kg) orally once daily, for a maximum of 3 days. See dosing chart for dosage directions.

Dosage Directions: For oral use in cats ≥ 5.5 lbs and ≥ 4 months of age; for up to a maximum of 3 days. Tablets are not scored and should not be broken.

Body weight | 6 mg ONSIOR (robenacoxib) Tablet
5.5 to 13.2 lbs (2.5 to 6 kg) | 1 whole tablet once daily
13.3 to 26.4 lbs (6.1 to 12 kg) | 2 whole tablets once daily

Do not use in cats weighing less than 5.5 lbs, as cats less than 5.5 lbs cannot be accurately dosed.

The first dose should be administered approximately 30 minutes prior to surgery, at the same time as the pre-anesthetic agents are given.

ONSIOR tablets may be given with or without food.

In cats ≥ 5.5 lbs and ≥ 4 months of age, subsequent doses can be given via the oral tablet, or interchanged with subcutaneous injection for a maximum of 3 total ONSIOR doses over 3 days, not to exceed one dose per day (see Animal Safety and the ONSIOR injection package insert).

Note the dose of ONSIOR tablets and ONSIOR injection are different.

If a second and third tablet dose is dispensed to the client to administer at home, doses should be dispensed in the dispensing envelope with the attached Information for Owner Sheet intact. Do not remove Information for Cat Owner Sheet. Record when the first dose was administered on the dispensing envelope. Cats weighing ≥ 13.3 lbs may require two blister cards, each dispensed in an individual dispensing envelope.

Contraindications:

ONSIOR tablets should not be used in cats that have a hypersensitivity to robenacoxib or known intolerance to NSAIDs.

Warnings:

Not for use in humans. Keep this and all medications out of reach of children. Consult a physician in case of accidental ingestion by humans. For oral use in cats only.

All cats should undergo a thorough history and physical examination before the initiation of NSAID therapy. Appropriate laboratory tests should be conducted to establish hematological and serum biochemical baseline data prior to administration of an NSAID.

Owners should be advised to observe for signs of potential drug toxicity (see Adverse Reactions and Animal Safety) and be given an “Information for Cat Owners” Sheet about ONSIOR tablets.

Do not administer ONSIOR tablets or injection in conjunction with any other oral or injectable NSAID or corticosteroid.

Precautions:

When using NSAIDS such as ONSIOR, the use of fluid therapy during surgery is recommended to decrease potential renal complications (see Adverse Reactions, Post-Approval Experience).

Appetite should be monitored in cats receiving ONSIOR.

Stop administration of ONSIOR if appetite decreases or if the cat becomes lethargic.

The use of ONSIOR tablets has not been evaluated in cats younger than 4 months of age and weighing less than 5.5 lbs, cats used for breeding, or in pregnant or lactating cats. Cats receiving ONSIOR should weigh at least 5.5 lbs.

The use of ONSIOR in cats with cardiac disease has not been studied. ONSIOR has been shown to prolong the QT interval.

As a class, cyclo-oxygenase inhibitory NSAIDs may be associated with gastrointestinal, renal, and hepatic toxicity. Sensitivity to drug-associated adverse events varies with the individual patient. Cats that have experienced adverse reactions from one NSAID may experience adverse reactions from another NSAID. Patients at greatest risk for adverse events are those that are dehydrated, on concomitant diuretic therapy, or those with existing renal, cardiovascular, and/or hepatic dysfunction. Anesthetic drugs may affect renal perfusion; approach concomitant use of anesthetics and NSAIDs cautiously. Appropriate monitoring procedures (including ECG, blood pressure, and temperature regulation) should be employed during all surgical procedures. The use of parenteral fluids during surgery is recommended to decrease potential renal complications when using NSAIDs perioperatively.

If additional pain medication is needed after a daily dose of ONSIOR, a non-NSAID/non-corticosteroid class of analgesic may be necessary. Concurrent administration of potentially nephrotoxic drugs should be carefully approached and monitored. NSAIDs may inhibit prostaglandins which maintain normal homeostatic function. Such anti-prostaglandin effects may result in clinically significant disease in patients with underlying or pre-existing disease that has not been previously diagnosed. NSAIDs possess the potential to produce gastrointestinal ulcerations and/ or gastrointestinal perforations. Do not use ONSIOR concomitantly with other anti-inflammatory drugs, such as NSAIDs or corticosteroids. Consider appropriate washout times when switching from one NSAID to another or when switching from corticosteroid use to NSAID use. ONSIOR tablets and ONSIOR injection are safe to use interchangeably when given once a day for a maximum of 3 days in cats ≥ 4 months of age and ≥ 5.5 lbs.

Note the dose of ONSIOR tablets and ONSIOR injection are different.

The use of concomitantly protein-bound drugs with ONSIOR has not been studied in cats. Commonly used protein-bound drugs include cardiac, anticonvulsant and behavioral medications. The influence of concomitant drugs that may inhibit metabolism of ONSIOR has not been evaluated. Drug compatibility should be monitored in patients requiring adjunctive therapy. Concurrent medications used during the field study with ONSIOR tablets included antiparasiticides, anesthetics, pre-anesthetic medications, and antibiotics.

The effect of cyclo-oxygenase inhibition and the potential for thromboembolic occurrence or a hypercoagulable state has not been evaluated. It is unknown whether cats with a history of hypersensitivity to ß lactam drugs will exhibit hypersensitivity to ONSIOR. Robenacoxib is poorly soluble in water and in acid solutions readily degrades to form γ-lactam. In cats, lactam is a metabolite of robenacoxib. Additionally, lactam is a degradation product that increases over the shelf-life of the tablets. Neurologic signs have been associated with the use of ß lactam drugs; it is unknown if the lactam in robenacoxib may cause similar neurologic signs (see Animal Safety). Occurrences of seizures, ataxia, and nystagmus have been associated with the use of ONSIOR.

Robenacoxib may prolong the QT interval; the associated risk of developing ventricular arrhythmia is unknown. The use of robenacoxib with other drugs shown to prolong the QT interval is not recommended. Commonly used drugs that prolong the QT interval include antihistamines, prokinetic drugs, and certain anesthetic drugs. As a class, it is unknown if the use of NSAIDs in asthmatic cats can cause acute exacerbations, as seen in some humans.

Adverse Reactions:

In a controlled field study, a total of 249 male and female cats representing 6 breeds, 6 months to 13 years old, weighing 5.5 – 15 lbs were included in the field safety analysis. The following table shows the number of cats exhibiting each observation.

Adverse Reactions in the Postoperative Pain Field Study^1
 | ONSIOR 6 mg Tablets for Cats | Placebo
Adverse Reaction | (robenacoxib); n = 167 | (vehicle control); n = 82
Incision site bleeding | 7 | 1
Incision site infection | 6 | 2
Inappetance, weight loss | 4 | 2
Decreased activity, lethargy | 4 | 1
Vomiting | 4 | 1
Cystitis, hematuria | 3 | 0
Hematachezia, diarrhea | 3 | 1
Hair loss, excoriation, bruising | 2 | 0
Respiratory, cardiac arrest | 1 | 0
Incoordination, weakness | 1 | 1
Death | 0 | 1
^1 Cats may have experienced more than one of these signs during the study.

The most commonly reported adverse reactions were surgical site bleeding, infected surgery sites, lethargy, vomiting and inappetance. Changes in the clinical pathology values were not considered clinically significant.

Post Approval Experience (2015)

The following adverse events are based on voluntary, post approval reporting. Not all adverse events are reported to FDA/CVM. It is not always possible to reliably estimate the adverse event frequency or establish a causal relationship to product exposure using these data. The signs reported are listed in decreasing order of reporting frequency:

Anorexia, depression/ lethargy, vomiting, elevated BUN, elevated creatinine, renal insufficiency/ failure, diarrhea, weight loss, dehydration.

In some cases, death has been reported. Some of these cases involved patients that developed renal failure/renal insufficiency.

To report suspected adverse drug events and for technical assistance, contact Elanco US Inc. at 1-888-545-5973.

For additional information about adverse drug experience reporting for animal drugs, contact FDA at 1-888-FDA-VETS or online at http://www.fda.gov/reportanimalae

Information for Cat Owners:

ONSIOR, like other drugs of its class, is not free from adverse reactions. Owners should be advised of the potential for adverse reactions and be informed of the clinical signs associated with drug intolerance. Adverse reactions may include vomiting, diarrhea, decreased appetite, dark or tarry stools, increased water consumption, increased urination, anemia, yellowing of gums, skin or white of the eye due to jaundice, lethargy, incoordination, seizure, or behavioral changes. Serious adverse reactions associated with this drug class can occur without warning and may result in death (see Warnings and Adverse Reactions). Owners should be advised to discontinue ONSIOR tablets and contact their veterinarian immediately if signs of intolerance are observed. The vast majority of patients with drug related adverse reactions have recovered when the signs are recognized, the drug is withdrawn, and veterinary care, if appropriate, is initiated.

Clinical Pharmacology:

In an inflammation model in cats, robenacoxib had analgesic, anti-inflammatory and anti-pyretic actions with a rapid onset of action (0.5 h).^1 In an in vitro whole blood assay in cats, robenacoxib demonstrated selective COX-2 inhibition.^2 The clinical relevance of this data has not been shown. Robenacoxib is an analog of diclofenac.

Absorption

After oral administration of robenacoxib tablets at 1 mg/kg without food, peak blood concentrations are attained rapidly with a median Tmax of 0.5 h, a mean Cmax of 1159 ng/ml and a mean AUC of 1337 ng.h/ml.

Co-administration of robenacoxib tablets with one third of the daily food ration produced no change in median Tmax (0.5 h), mean Cmax (1201 ng/ml) or mean AUC (1383 ng.h/ml). Co-administration of robenacoxib tablets with the entire daily food ration produced no delay in median Tmax (0.5 h), but a lower mean Cmax (691 ng/ml) and a lower mean AUC (1069 ng.h/ml). The systemic mean bioavailability of robenacoxib tablets was 49% without food. The pharmacokinetics of robenacoxib does not differ between male and female cats.

Distribution

Robenacoxib has a relatively small volume of distribution (mean Vss = 190 ml/kg) and is highly bound to plasma proteins (>99%). Robenacoxib persists longer in the inflammatory exudate of a tissue cage model than in blood. The median robenacoxib elimination half-life in exudate was about 27 hours versus 2.5 hours for blood.

Metabolism

Robenacoxib is extensively metabolized by the liver in cats. The systemic exposure of lactam metabolite is about 25% of robenacoxib exposure following oral administration to fed cats. Further, the systemic exposure to lactam appears to be two-fold greater in fed cats than fasted cats. Apart from one lactam metabolite, the identity of other metabolites is not known in cats.

Elimination

Robenacoxib is rapidly cleared from blood (mean clearance [CL] = 0.44 L kg/h) with an elimination mean half-life (t1/2) of 1.1 hours after intravenous administration. After oral administration of tablets, the terminal mean t1/2 from blood was 1.7 hours. Elimination, occurs predominantly through the biliary route (fecal and urinary excretion are 60 and 16.5% respectively).

Animal Safety:

21 Day Target Animal Safety Study: In a 21-day laboratory tolerance study, 8 month-old healthy, DSH cats (4/sex/group) were administered robenacoxib at a dose of 0 mg/kg or 24 mg/kg/day (10X the maximum exposure based on the single, 6 mg tablet size). All cats survived to study termination. Vomiting and decreased activity was noted in some of the treated cats. Two cats in the 10X group exhibited abnormal rear limb neurologic function. One of these cats also exhibited a head tilt and nystagmus at the end of the study. Mean food consumption was less in the 10X group. The mean kidney weights were lower in the 10X group compared to the control group; and the mean thymus weights were also lower in the 10X group compared to the controls. Two cats in the 10X group had chronic interstitial nephritis on histopathology. One 10X cat had a focal cecal/large intestinal erosion. One 10X cat and one control cat had periportal, multifocal necrosis in one lobe of the liver. There were four 10X cats and 2 control cats with renal tubular degeneration. Under the conditions of this study, robenacoxib was well tolerated when administered at 24 mg/kg/day for 21 days, except for 2 cats in the 10X group with neurologic signs.

42 Day Target Animal Safety Study:

In a 42 day study, 8 month-old, healthy cats were administered robenacoxib at 0, 2, 6 or 10 mg/kg/twice daily. Small thymuses were noted in all robenacoxib-treated groups with corresponding organ weight decreases and/or atrophic changes on histopathology. There was a decrease in the kidney weights in the 10 mg/kg/twice daily-group compared to the controls. Vomiting was the most common adverse reaction noted in the treated cats. An adequate safety margin was demonstrated for ONSIOR tablets when administered under the conditions of this 42-day study.

6 Month Target Animal Safety Study:

In a 6 month study, 8 month-old, healthy cats (4/sex/group) were administered robenacoxib at 0, 1X (2.4 mg/kg), 3X (7.2 mg/kg) or 5X (12 mg/kg) once daily. One 5X cat had clonic seizures on Day 115 and was ataxic on Day 175. One 5X cat had skin cold to the touch on Day 106. One cat in the 1X group experienced urethral obstruction/FLUTD. Vomiting, decreased activity, injected sclera and soft stools were the most common adverse reactions observed in the treated groups. Soft stools and injected sclera were also observed in the control group.

The mean body weights in the 1X and 3X groups were lower than the controls from Day 21 – Day 182; and lower in the 5X group from Day 28 – Day 182. There was a clear dose-related and possibly time-related increase in the QTc interval at Day 41 and Day 175, particularly in the 3X and 5X groups, no other ECG abnormalities were noted.

There was no obvious accumulation in Cmax or AUC between Days 1, 31 and 171, and there was no apparent difference in parameters between males and females. The following parameters were calculated for the 1X dosage: Tmax was 0.5 h (median), the dose-normalized mean Cmax was 668 ng/mL and the dose-normalized mean area under the curve (AUC(0-inf)) was 902 h*ng/mL. Similarly, the following parameters were calculated for the 3X dosage: Tmax was 0.5 h (median), the dose-normalized mean Cmax was 1019 ng/mL and the dose-normalized mean area under the curve (AUC(0-inf)) was 1394 h*ng/mL. For the 5X dosage the following parameters were calculated: Tmax was 1.0 h (median), the dose-normalized mean Cmax was 1198 ng/mL and the dose-normalized mean area under the curve (AUC(0-inf)) was 1884 h*ng/mL. A post hoc analysis of PK parameters revealed that dose normalized Cmax and AUC were greater than dose proportional.

The mean kidney weights were lower in all robenacoxib-treated groups. One 5X cat with decreased kidney weight and size also had transient increases in BUN and creatinine. There were transient increases in AST, amylase, and ALT in the 3X and 5X cats from Day 30 – Day 183. There was an increased severity of the tubular degeneration/regeneration in the kidneys of two 1X and two 5X cats with inflammation, papillary necrosis and papillary mineralization.

An increased incidence of minimal to mild Kupffer cell pigmentation was observed in the livers of all robenacoxib-treated cats; however, no hepatocellular damage was noted on histopathology. One 5X cat had a focal, minimal ulcer of the gastric fundus (peptic and parietal cells).

This 6 month safety study supports the safe use of ONSIOR tablets for the control of postoperative pain and inflammation associated with orthopedic surgery, ovariohysterectomy and castration in cats for a maximum of 3 days.

Interchangeable Use Safety Study:

ONSIOR was administered orally (6 mg tablets) and subcutaneously (20 mg/mL solution) to 4-month old healthy cats at 0, 1, 2, and 3 times the labeled doses (1X = 2.4 mg/kg/day orally based on the inherent tablet dose band or 2.0 mg/kg/day subcutaneously). Interchangeable use was evaluated by alternating three 7-day oral tablet/3-day subcutaneous injection cycles followed by one final 7-day oral tablet dosing cycle. All cats survived until study termination. Findings included: elevated creatine kinase levels on Days 13 and 37, soft stools, histologic observation of a minimal oral (tongue) ulceration in a 1X cat, injection site edema for up to 120 hours prior to resolution, and a prolonged QT interval in treated cats as compared to the controls on Day 36. There was a dose dependent and statistically significant increase in the QT interval at all three ONSIOR tablets/ONSIOR injection treatment levels. It is unknown if the increased QT interval suggests an elevated risk of ventricular arrhythmia or torsade de pointes in cats. In addition, a longer PR interval was noted in 1X group females on Day 36 compared to the controls. One 2X cat vomited twice during the last 2 dosing days. Histologically, the injection sites had minimal or mild, subacute/chronic inflammation. Inflammation at the injection sites was observed in both treated and control animals with a greater frequency in the higher dose groups than in the control and 1X groups. Dose-normalized AUC and concentration levels were higher following the oral route than the subcutaneous route. There was no significant accumulation following once daily administration. One 2X-treated cat had a 7-fold increase in buccal mucosal bleeding time (BMBT) during the treatment period compared to the pre-treatment value.

Effectiveness:

Effectiveness was demonstrated using ONSIOR tablets in a masked, placebo-controlled, multi-site field study involving client-owned cats. In this study, 249 cats presenting for ovariohysterectomy or castration in conjunction with an onychectomy (forelimbs only) were randomly administered ONSIOR tablets, or a placebo. Drug was administered approximately 30 minutes prior to surgery along with pre-anesthetic medications and continued once daily for two additional treatments. Effectiveness was evaluated in 244 cats and field safety was evaluated in 249 cats. A statistically significant difference in the proportion of treatment successes in the ONSIOR tablets treatment group (137/164 or 83.5%) compared to the placebo, vehicle control group (43/80 or 53.8%) was observed. Twenty-seven out of 164 robenacoxib cases (16.5%) and 37 out of 80 placebo cases (46.2%) were treatment failures. Statistically significant differences for pain elicited on palpation at the spay or castration incision site, behavior following social interaction and posture score at various post-surgical time points were also observed. The results of the field study demonstrate that ONSIOR tablets, when administered for a maximum of three days, are effective and well-tolerated for the control of postoperative pain associated with onychectomy, ovariohysterectomy and castration in cats.

How Supplied:

ONSIOR tablets are available as 6 mg round flavored tablets in blisters and are supplied in blister cards containing 3 tablets. The blister cards are supplied in a veterinary carton containing 10 blister cards and are to be dispensed 1 card per patient in an ONSIOR tablets dispensing envelope containing veterinary insert and owner information sheet, supplied with the product.

Storage Conditions:

Store at controlled room temperature, between 59° and 77°F (15-25°C).

Manufactured for: Elanco US Inc. Greenfield, IN 46140, USA

References:

^1Giraudel, J.M., King J.N., Jeunesse, E.C., Lees, P. & Toutain, P.L. (2008). Use of a pharmacokinetic/pharmacodynamic approach in the cat to determine a dosage regimen for the COX-2 selective drug robenacoxib. J Vet Pharmacol Ther 2009;32:18-30.

^2Giraudel, J.M., Toutain, P.L., King J.N., & Lees, P. Differential inhibition of cyclooxygenase isoenzymes in the cat by the COX-2 selective drug robenacoxib. J Vet Pharmacol Ther 2009;32:31-40.

Approved by FDA under NADA # 141-320
Onsior, Elanco and the diagonal bar logo are trademarks of Elanco or its affiliates.

INFORMATION FOR OWNERS/CAREGIVERS

onsior™
(robenacoxib)
6 mg Tablets for Cats

For Oral Use In Cats Only

Information for Cat Owners – You should read this information before starting your cat on ONSIOR tablets.

What is ONSIOR?

ONSIOR (robenacoxib) is a prescription non-narcotic, non-steroidal anti-inflammatory (NSAID) of the coxib class. ONSIOR (robenacoxib) is for the control of postoperative pain and inflammation associated with orthopedic surgery (declaw), ovariohysterectomy (spay) and castration (neuter) in cats greater than or equal to 5.5 pounds (2.5 kg) and greater than or equal to 4 months of age; for a maximum of 3 days. Do not use in cats less than 5.5 lbs.

Your cat may have received one or more doses of ONSIOR tablets or injection in the hospital. Your cat should not receive more than one dose a day, for a maximum of 3 total doses. Follow the instructions given to you by your veterinarian.

This summary contains important information about ONSIOR but does not take the place of instructions from your veterinarian. Talk to your veterinarian if you do not understand any of this information or if you want to know more about ONSIOR for cats.

What kind of results can I expect when my cat takes ONSIOR for postoperative pain and inflammation?

ONSIOR may help your cat to recover more comfortably by controlling postoperative pain and inflammation following orthopedic (declaw), ovariohysterectomy (spay), or castration surgery (neuter).

- Control of postoperative pain and inflammation may vary from cat to cat.
- Administer ONSIOR tablets according to your veterinarian‘s directions, for a maximum of 3 days.
- Consult your veterinarian if your cat appears to be uncomfortable.

What cats should not take ONSIOR?

Your cat should not be given ONSIOR if s/he:

- Has had an allergic reaction to robenacoxib, the active ingredient in ONSIOR for cats
- Has had an allergic reaction (such as hives, facial swelling, or red or itchy skin) to aspirin or other NSAIDs
- Is less than 5.5 lbs or less than 4 months of age
- Has a loss of appetite/decreased appetite
- Has bloody stool or vomit
- Is presently taking aspirin, other NSAIDs, or corticosteroids
- Has a pre-existing kidney or liver condition
- Has any condition predisposing to dehydration

ONSIOR tablets should only be given to cats.

People should not take ONSIOR tablets. Keep ONSIOR tablets and all medication out of reach of children. Call your physician immediately if you accidentally take ONSIOR tablets.

Tell your veterinarian about:

- Any side effects your cat has previously experienced from ONSIOR or other NSAIDs
- Any digestive upset (vomiting or diarrhea) your cat has had
- Any cardiovascular, kidney or liver disease your cat has had
- Any other medical problems or allergies that your cat has now or has had in the past
- All medications that you are giving your cat or plan to give your cat, including those you can get without prescription and any dietary supplements
- If you plan to breed your cat, or if your cat is pregnant or nursing

Talk to your veterinarian about:

- The surgery procedure performed on your cat
- What tests should be done before surgery and prior to administering ONSIOR
- The signs of postoperative pain or inflammation that may occur following surgery
- Normal events that can be expected after your cat undergoes surgery
- How often your cat may need to be examined by your veterinarian
- The risks and benefits of using ONSIOR

How to give ONSIOR tablets to your cat.

ONSIOR tablets should be given according to your veterinarian‘s instructions. Your veterinarian will tell you what amount of ONSIOR tablets is right for your cat. ONSIOR tablets should only be given once a day and for no longer than 3 days. ONSIOR tablets should not be broken. ONSIOR tablets should be given by mouth and may be given with or without food.

What are the possible side effects that may occur in my cat during therapy with ONSIOR tablets?

ONSIOR tablets may cause some side effects in individual cats. These are normally mild, but serious side effects have been reported in cats taking non-steroidal anti-inflammatory drugs (NSAIDs) including ONSIOR tablets. Serious side effects can result in death. It is important to stop the medication and contact your veterinarian immediately if you think your cat may have a medical problem or side effect while on ONSIOR tablets. If you have additional questions about possible side effects, talk with your veterinarian or call Elanco US Inc. at 1-888-545-5973.

Look for the possible following side effects that may indicate that your cat is having a problem:

- Decrease in appetite
- Vomiting
- Change in bowel movements such as diarrhea or change in stool color
- Change in drinking or urination
- Change in behavior, such as depression or restlessness

If any of the above signs are noticed in your cat, stop administering ONSIOR tablets and call your veterinarian.

Can ONSIOR tablets be given with other medications?

ONSIOR tablets should not be given with other non-steroidal anti-inflammatory drugs (NSAIDs – i.e. aspirin, meloxicam) or corticosteroids (i.e. prednisone).

Always tell your veterinarian about all medications that you have given your cat in the past, and any medications that you are planning to give with ONSIOR tablets.

What can I do in case my cat eats more than the prescribed amount of ONSIOR tablets?

Contact your veterinarian immediately if your cat eats more than the prescribed amount of ONSIOR tablets.

What else should I know about ONSIOR tablets?

This sheet provides a summary of information about ONSIOR tablets. If you have any questions or concerns about ONSIOR or postoperative pain and inflammation, talk to your veterinarian.

As with all prescribed medications, ONSIOR tablets should only be given to the cat for which they are prescribed. They should be given to your cat only for the condition for which they were prescribed, at the prescribed dose, as directed by your veterinarian.

Approved by FDA under NADA # 141-320

Onsior, Elanco and the diagonal bar logo are trademarks of Elanco or its affiliates.

© 2024 Elanco or its affiliates

Revised: June 2024

ElancoTM

Principal Display Panel - Onsior Cat 6 mg Dispensing Envelope

onsior™

(robenacoxib)

6 mg per
tablet

Record date of when oral or
injectable dose(s) given
in hospital and when next
dose(s) are due.

Check box when dose is given.

6 mg

For oral use
in cats only

≥ 5.5 pounds and

≥ 4 months of age

Date of Administration,
Onsior given on

Day 1

Day 2

Day 3

Principal Display Panel - Onsior Cat 6 mg Carton Label

Indication: For the control of postoperative pain and inflammation associated
with orthopedic surgery, ovariohysterectomy and castration, in cats ≥
5.5 lbs (2.5 kg) and ≥ 4 months of age; for up to a maximum of 3 days.

See product insert for complete information.

onsior™

(robenacoxib)

6 mg

6 mg per
tablet

Keep this and all drugs out
of the reach of children.

Elanco™

Indication: For the control of postoperative pain
and inflammation associated with orthopedic
surgery, ovariohysterectomy and castration, in
cats ≥ 5.5 lbs (2.5 kg) and ≥ 4 months of age;
for up to a maximum of 3 days.

See product insert for complete information.

onsior™

(robenacoxib)

6 mg

6 mg per
tablet

Keep this and all drugs out
of the reach of children.

Elanco™